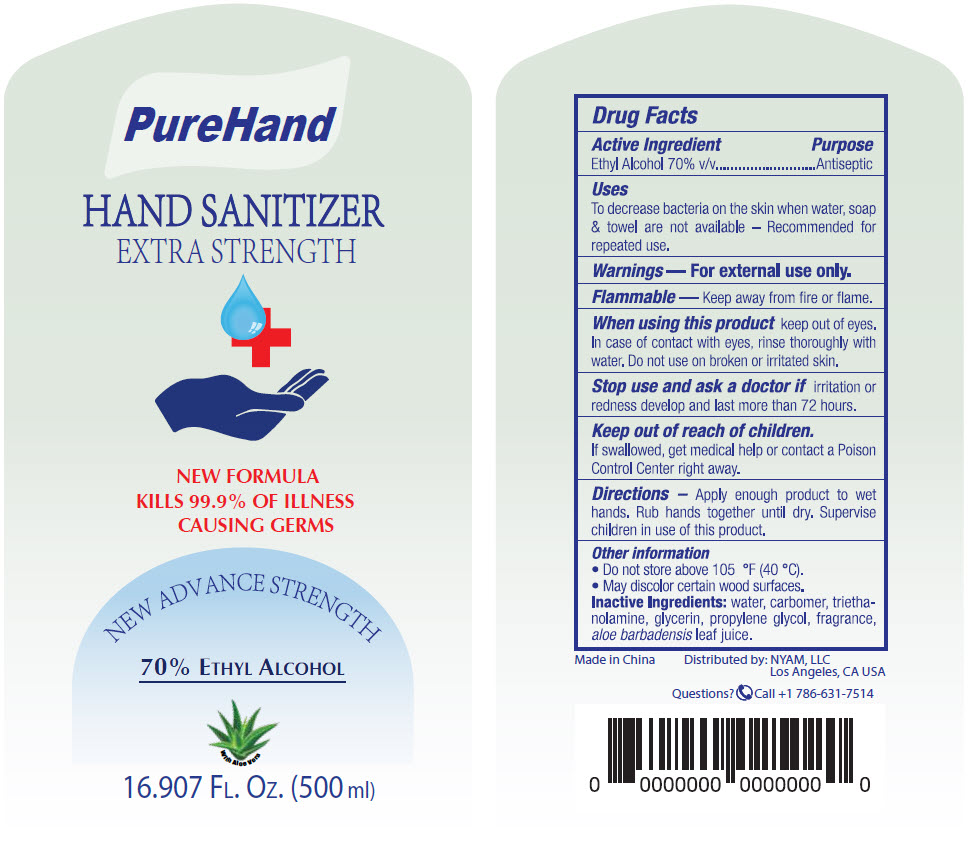 DRUG LABEL: Hand Sanitizer
NDC: 77294-123 | Form: LIQUID
Manufacturer: NYAM LLC
Category: otc | Type: HUMAN OTC DRUG LABEL
Date: 20200507

ACTIVE INGREDIENTS: ALCOHOL 70 mL/100 mL
INACTIVE INGREDIENTS: water; carbomer homopolymer, unspecified type; trolamine; glycerin; propylene glycol; aloe vera leaf

Hand Sanitizer

Drug Facts

Active Ingredient

Ethyl Alcohol 70% v/v

Purpose

Antiseptic

Uses

To decrease bacteria on the skin when water, soap & towel are not available – Recommended for repeated use.

Warnings

For external use only.

Flammable — Keep away from fire or flame.

When using this product keep out of eyes. In case of contact with eyes, rinse thoroughly with water. Do not use on broken or irritated skin.

Stop use and ask a doctor if irritation or redness develop and last more than 72 hours.

Keep out of reach of children.

If swallowed, get medical help or contact a Poison Control Center right away.

Directions

Apply enough product to wet hands. Rub hands together until dry. Supervise children in use of this product.

Other information

- Do not store above 105 °F (40 °C).
- May discolor certain wood surfaces.

Inactive Ingredients

water, carbomer, triethanolamine, glycerin, propylene glycol, fragrance, aloe barbadensis leaf juice.

Questions?

Call +1 786-631-7514

Distributed by: NYAM, LLC
Los Angeles, CA USA

PRINCIPAL DISPLAY PANEL - 500 ml Bottle Label

PureHand

HAND SANITIZER
EXTRA STRENGTH

NEW FORMULA
KILLS 99.9% OF ILLNESS
CAUSING GERMS

NEW ADVANCE STRENGTH

70% ETHYL ALCOHOL

16.907 FL. OZ. (500 ml)